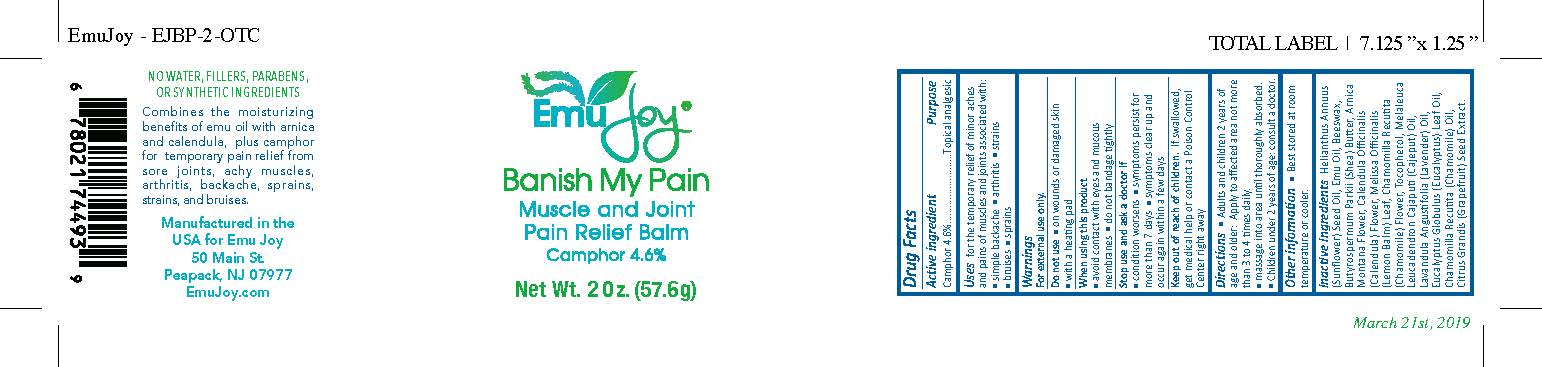 DRUG LABEL: Banish My Pain
NDC: 72895-081 | Form: OINTMENT
Manufacturer: LAIDEN MONTANA EMU PRODUCTS
Category: otc | Type: HUMAN OTC DRUG LABEL
Date: 20190506

ACTIVE INGREDIENTS: CAMPHOR (NATURAL) 2.576 g/60 mL
INACTIVE INGREDIENTS: SUNFLOWER OIL; EMU OIL; MATRICARIA CHAMOMILLA FLOWERING TOP; EUCALYPTUS OIL; MELISSA OFFICINALIS LEAF; LAVENDER OIL; CHAMOMILE FLOWER OIL; GRAPEFRUIT SEED OIL; YELLOW WAX; SHEA BUTTER; ARNICA MONTANA FLOWER; CALENDULA OFFICINALIS FLOWER; TOCOPHEROL; CAJUPUT OIL

Banish My Pain

Active ingredient

Camphor 4.6%

Purpose

Topical analgesic

Uses

for the temporary relief of minor aches and pains of muscles and joints associated with:

- simple backache
- arthritis
- strains
- bruises
- sprains

Warnings

For external use only.

Do not use

- on wounds or damaged skin
- with a heating pad

When using this product

- avoid contact with eyes and mucous membranes
- do not bandage tightly

Stop use and ask a doctor if

- condition worsens
- symptoms persist for more than 7 days
- symptoms clear up and occur again within a few days

Keep out of reach of children.

If swallowed, get medical help or contact a Poison Control Center right away

Directions

- Adults and children 2 years of age and older: Apply to affected area not more than 3 to 4 times daily.
- massage into area until thoroughly absorbed
- Children under 2 years of age: consult a doctor.

Other information

- Best stored at room temperature or cooler.

Inactive ingredients

Helianthus Annuus (Sunflower) Seed Oil, Emu Oil, Beeswax, Butyrospermum Parkii (Shea) Butter, Arnica Montana Flower, Calendula Officinalis (Calendula) Flower, Melissa Officinalis (Lemon Balm) Leaf, Chamomilla Recutita (Chamomile) Flower, Tocopherol, Melaleuca Leucadendron Cajaputi (Cajeput) Oil, Lavandula Angustifolia (Lavender) Oil, Eucalyptus Globulus (Eucalyptus) Leaf Oil, Chamomilla Recutita (Chamomile) Oil, Citrus Grandis (Grapefruit) Seed Extract.